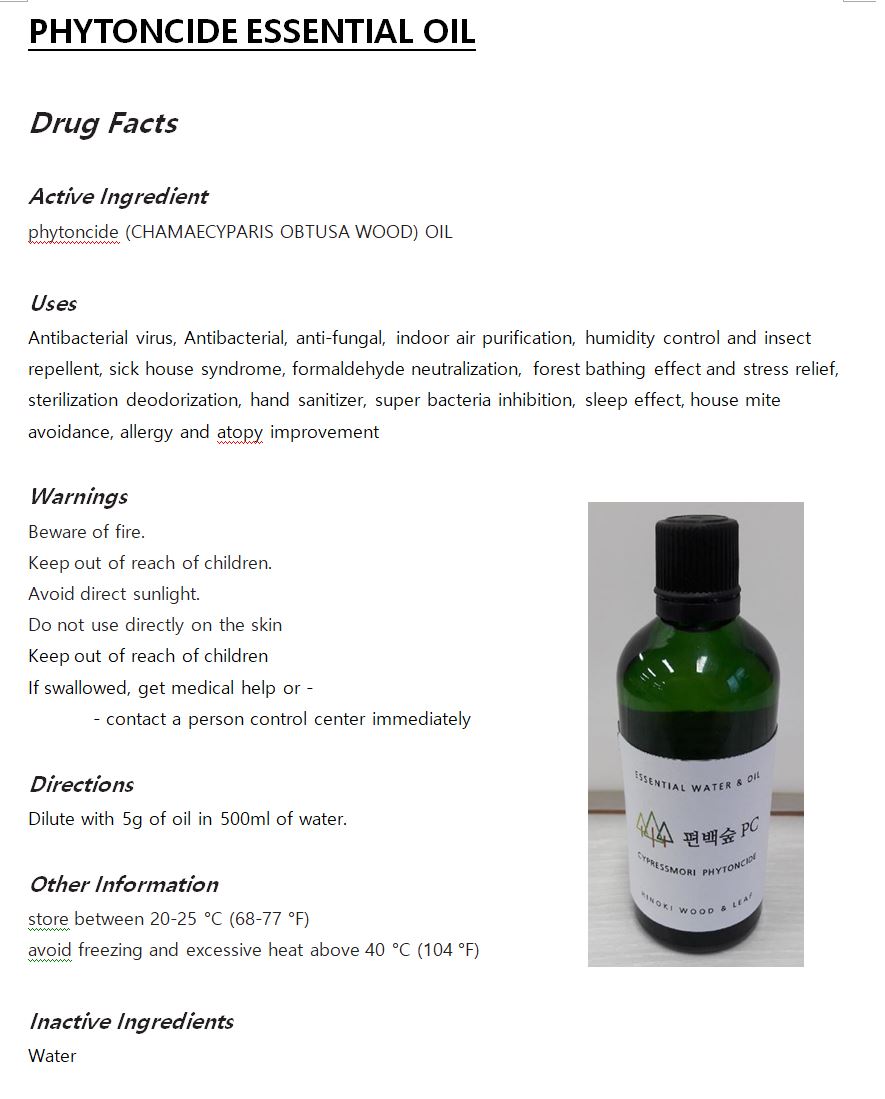 DRUG LABEL: PHYTONCIDE ESSENTIAL
NDC: 73645-0001 | Form: OIL
Manufacturer: DONGYANG SPECIAL WOOD CORPORATION
Category: otc | Type: HUMAN OTC DRUG LABEL
Date: 20230126

ACTIVE INGREDIENTS: CHAMAECYPARIS OBTUSA WOOD OIL 99.9 g/100 mL
INACTIVE INGREDIENTS: WATER

ACTIVE INGREDIENT

phytoncide (CHAMAECYPARIS OBTUSA WOOD) OIL

INACTIVE INGREDIENT

Water

PURPOSE

Antibacterial, anti-fungal, indoor air purification, humidity control and insect repellent, sick house syndrome, formaldehyde neutralization, forest bathing effect and stress relief, sterilization deodorization, hand sanitizer, super bacteria inhibition, sleep effect, house mite avoidance, allergy and atopy improvement

WARNINGS

Beware of fire.
Keep out of reach of children.
Avoid direct sunlight.
Do not use directly on the skin

Keep Out of Reach of Children

DOSAGE AND ADMINISTRATION

for topical use only

INDICATIONS AND USAGE

Dilute with 5g of oil in 500ml of water